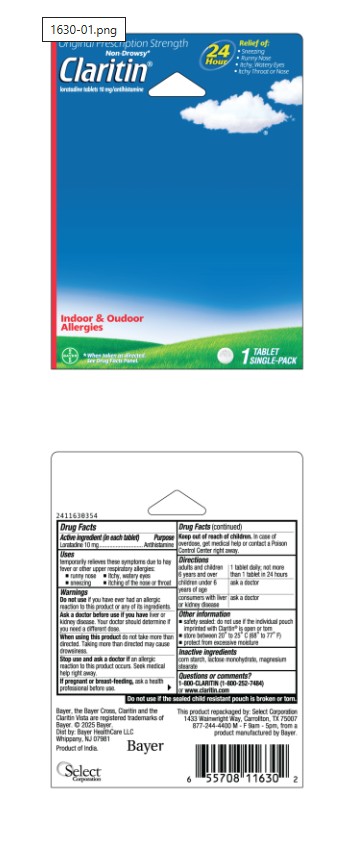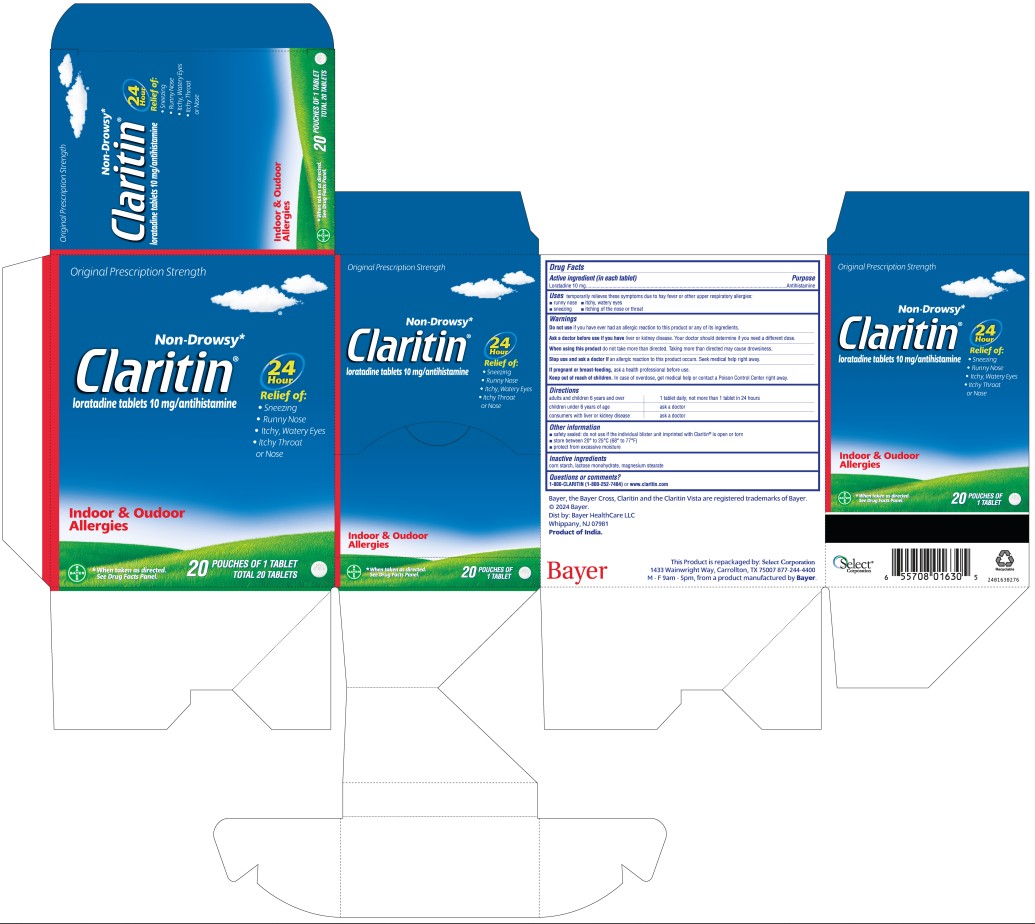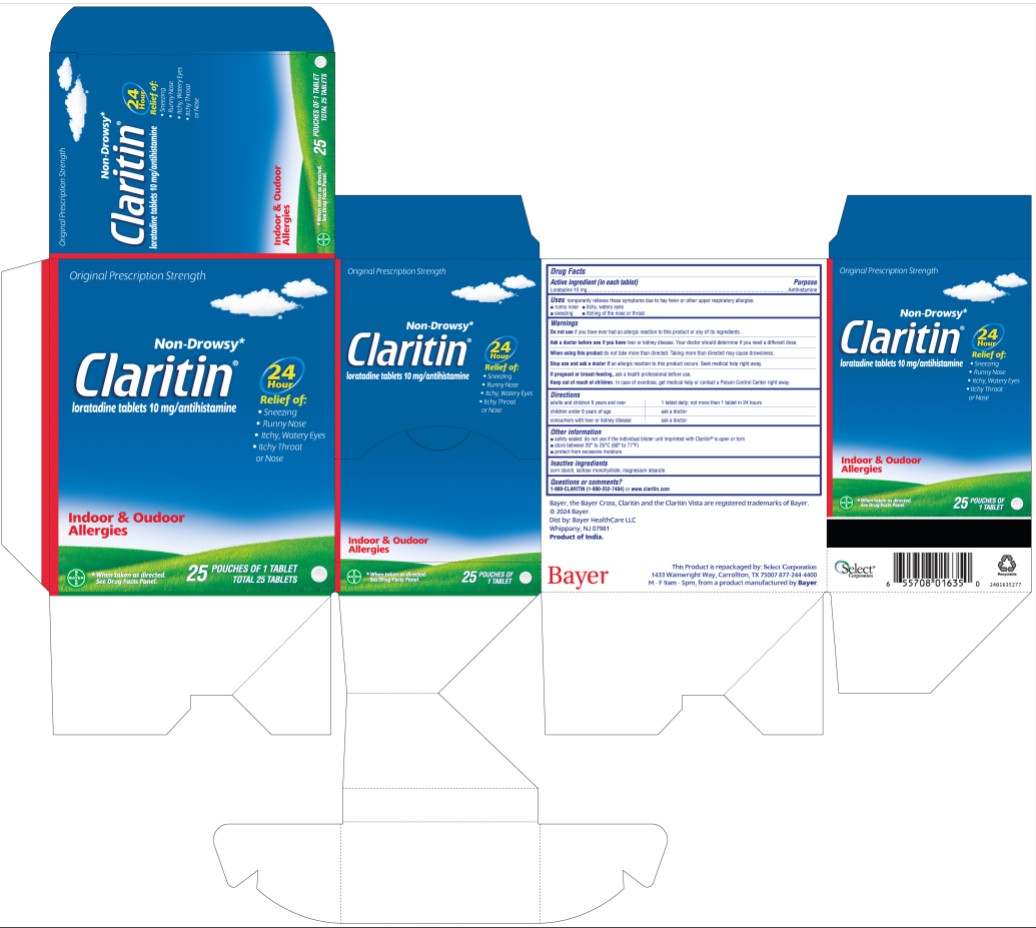 DRUG LABEL: Claritin
NDC: 85237-1630 | Form: TABLET
Manufacturer: Select Consumer Group
Category: otc | Type: HUMAN OTC DRUG LABEL
Date: 20251228

ACTIVE INGREDIENTS: LORATADINE 10 mg/1 1
INACTIVE INGREDIENTS: LACTOSE MONOHYDRATE; MICROCRYSTALLINE CELLULOSE; MAGNESIUM STEARATE; SODIUM STARCH GLYCOLATE TYPE A CORN

Drug Facts

Active ingredient (in each tablet)

Loratadine, 10 mg USP

Purpose

Antihistamine

Uses

Temporarily relieves these symptoms due to hay fever or other upper respiratory allergies:

■ runny nose ■ sneezing

■ itchy, watery eyes ■ itching of the nose or throat

Warnings

DO NOT USE

Do not useif you have ever had an allergic reaction to this product or any of its ingredients.

Ask a doctor before use if you haveliver or kidney disease. Your doctor should determine if you need a different dose.

When using this product

When using this productdo not take more than directed. Taking more than directed may cause drowsiness.

Stop use

Stop use and ask a doctor ifan allergic reaction to this product occurs. Seek medical help right away.

If pregnant or breast-feeding, ask a health professional before use.

Keep out of reach of children. In case of overdose, get medical help or contact a Poison Control Center right away (1-800-222-1222).

Directions

adults and children 6 years and over | 1 tablet daily; not more than 1 tablet in 24 hours
children under 6 years of age | ask a doctor
consumers with liver or kidney disease | ask a doctor

Other information

■ store at 20º -25º C (68º -77º F) (see USP Controlled Room Temperature)

INACTIVE INGREDIENT

Inactive ingredientslactose monohydrate, magnesium stearate, microcrystalline cellulose, sodium starch glycolate

Questions or comments?

1-800-CLARITIN (1-800-252-7484) or www.claritin.com